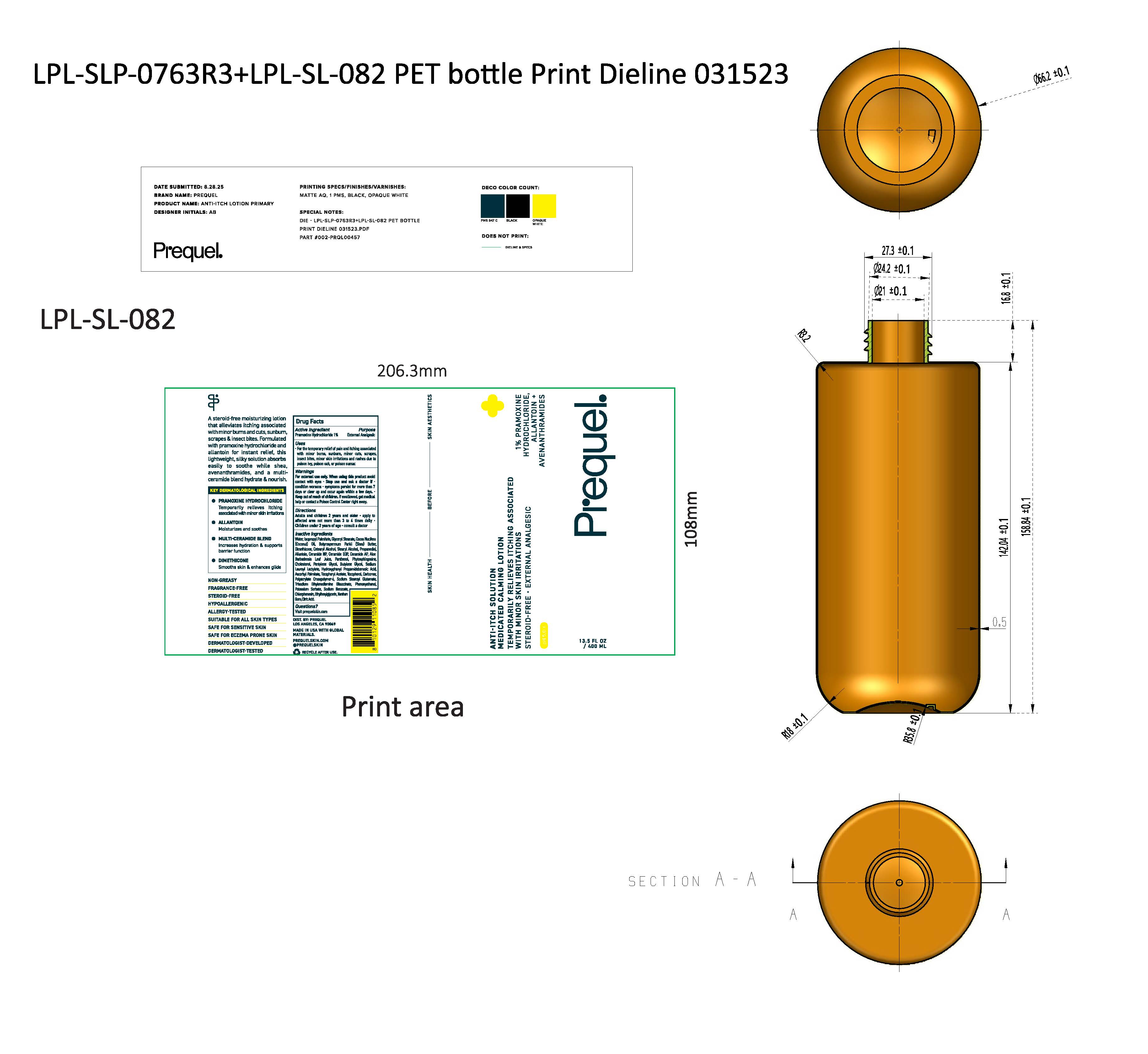 DRUG LABEL: Prequel Anti-Itch Solution Medicated Calming
NDC: 82800-200 | Form: LOTION
Manufacturer: The Center Brands, LLC
Category: otc | Type: HUMAN OTC DRUG LABEL
Date: 20251204

ACTIVE INGREDIENTS: PRAMOXINE HYDROCHLORIDE 1 g/100 g
INACTIVE INGREDIENTS: WATER; ISOPROPYL PALMITATE; GLYCERYL STEARATE SE; COCOS NUCIFERA (COCONUT) OIL; BUTYROSPERMUM PARKII (SHEA) BUTTER; DIMETHICONE; STEARYL ALCOHOL; PROPANEDIOL; CETEARYL ALCOHOL; ALLANTOIN; CERAMIDE NP; CERAMIDE AP; ALOE BARBADENSIS LEAF JUICE; PANTHENOL; PHYTOSPHINGOSINE; PHENOXYETHANOL; CHOLESTEROL; PENTYLENE GLYCOL; BUTYLENE GLYCOL; SODIUM LAUROYL LACTYLATE; ASCORBYL PALMITATE; .ALPHA.-TOCOPHEROL ACETATE, D-; CARBOMER; POLYACRYLATE CROSSPOLYMER-6; SODIUM STEAROYL GLUTAMATE; TRISODIUM ETHYLENEDIAMINE DISUCCINATE; POTASSIUM SORBATE; SODIUM BENZOATE; CHLORPHENESIN; ETHYLHEXYLGLYCERIN; XANTHAN GUM; ANHYDROUS CITRIC ACID

Prequel Anti-Itch Solution Medicated Calming Lotion

Purpose

External Analgesic

Active Ingredients

Pramoxine Hydrochloride 1.0%

Uses

For the temporary relief of pain and itching associated with minor burns, sunburn, minor cuts, scrapes, insect bites, minor skin irritation and rashed ue to poison ivy, poison oak or poison sumac

Warnings

Fox external use only.

When using this product do not get into eyes

Stop use and ask a doctor if condition worsens

symptoms last more than 7 days or clear up and occur again within a few days

If swallowed, get medial help or contact a Poison Control Center right away.

Keep out of reach of children.

Directions

Adulta and children 2 years and older- apply to affected area not more than 3 to 4 times daily. Children under 2 years of age consult a doctor

Inactive ingredients

Water, Isopropyl Palmitate, Glyceryl Stearate, Cocos Nucifera (Coconut) Oil, Butyrospermum Parkii (Shea) Butter, Dimethicone, Cetearyl Aclohol, Stearyl Alcohol, Propanediol, Allantoin, Ceramide NP, Ceramide EOP, Ceramide AP, Aloe Barbadensis Leaf Juice, Panthanol, Phytosphingosine, Cholesterol, Pentylene Glycol, Butylene Glycol, Sodium Lauroyl Lactylate, Hyroxyphenyl Propamidobenzoic Acid, Ascorbyl Palmitate, Tocopheryl Acetate, Tocopherol, Carbomer, Polyacrylate Crosspolymer-6, Sodium Stearoyl Glutamate, Trisodium Ethylenediamine Disuccinate, Phenoxyethanol, Potassium Sorbate, Sodium Benzoate, Chlorphenesin, Ethylhexylglycerin, Xanthan Gum, Citric Acid

Questions?

Visit prequelskin.com